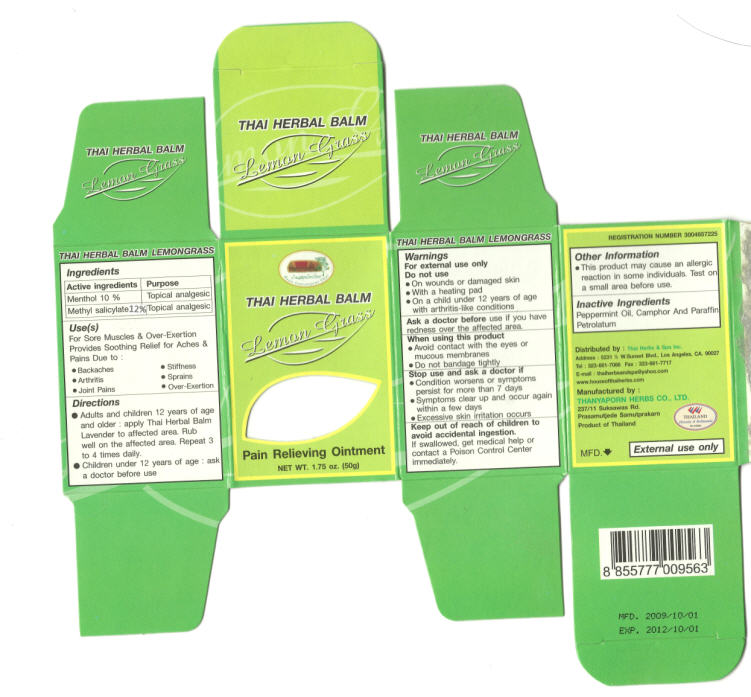 DRUG LABEL: Thai Herbal Balm Lemon Grass
                
NDC: 75978-3048 | Form: OINTMENT
Manufacturer: Thai Herb and Spa
Category: otc | Type: HUMAN OTC DRUG LABEL
Date: 20120726

ACTIVE INGREDIENTS: Menthol 5 g/50 g; Methyl Salicylate 6 g/50 g
INACTIVE INGREDIENTS: West Indian Lemongrass Oil 2.5 g/50 g; Peppermint Oil 2.5 g/50 g; Camphor (synthetic) 1.5 g/50 g; Paraffin 7.5 g/50 g; Petrolatum 27.5 g/50 g

Thai Herbal Balm Lemon Grass

Ingredients

Active Ingredients | Purpose
Menthol 10% | Topical analgesic
Methyl Salicylate 12% | Topical analgesic

Use(s)

For sore muscles and over-exertion.

Provides sooting relief for aches and pains due to:

- Backaches
- Arthritis
- Joint Pains
- Stiffness
- Sprains
- Over-exertion

Directions

- Adults and children 12 years of age and older : Apply Thai Herbal Balm Lemon Grass to affected area. Rub well on the affected area. Repeat 3 to 4 times daily.
- Children under 12 years of age: ask a doctor before use.

Warnings

For external use only

Do not use

- on wounds or damaged skin
- with a heating pad
- on a child under 12 years of age with arthritis-like conditions.

Ask a doctor before

use if you have redness over the affected area.

When using this product

- Avoid contact with the eyes or mucous membranes
- Do not bandage tightly

Stop use and ask a doctor if

- Condition worsens or symptoms persist for more than 7 days
- Symptoms clear up and occur again within a few days
- Excessive skin irritation occurs

Keep out of reach of children to avoid accidental ingestion.

If swallowed, get medical help or contact a Poison Control Center immediately.

Other Information

- This product may cause an allergic reaction in some individuals. Test on a small area before use.

Inactive Ingredients

Peppermint Oil, Camphor And Paraffin Petrolatum.

PRINCIPAL DISPLAY PANEL - 50g Jar

THAI HERBAL BALM

LEMON GRASS

PAIN RELIEVING OINTMENT

NET WT. 1.75 oz. (50g)